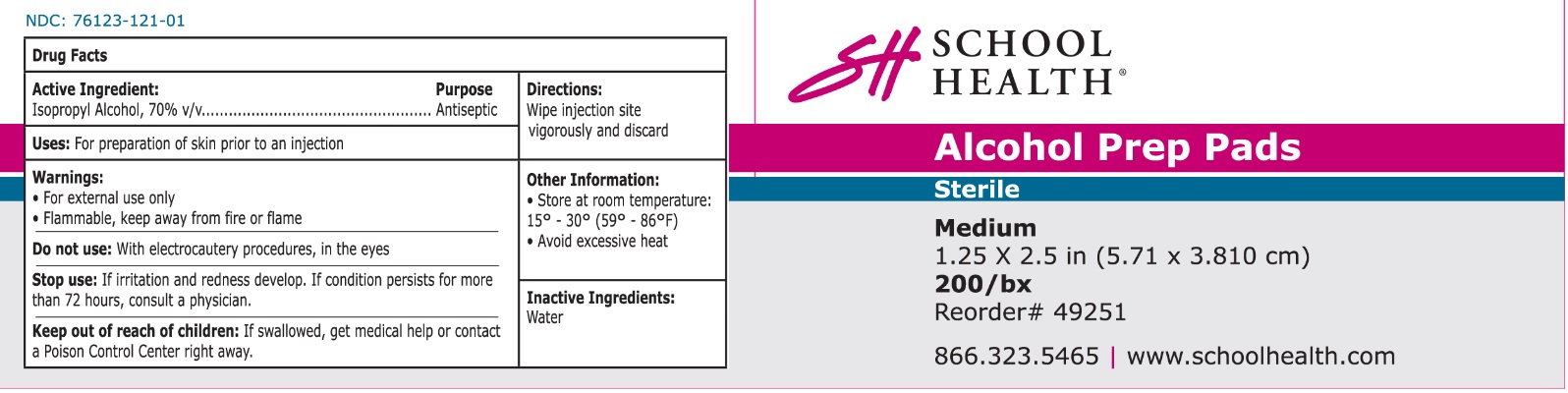 DRUG LABEL: School Health Sterile Alcohol Prep Pad
NDC: 76123-121 | Form: SWAB
Manufacturer: School Health Corporation
Category: otc | Type: HUMAN OTC DRUG LABEL
Date: 20251023

ACTIVE INGREDIENTS: ISOPROPYL ALCOHOL 0.7 mL/1 mL
INACTIVE INGREDIENTS: WATER

School Health Alcohol Prep Pad

Active Ingredient

Isopropyl Alcohol 70% v/v

Purpose

Antiseptic

Uses:

For preparation of skin pror to an injection

Warnings:

- For external use only
- Flammable, keep away from flame or fire

Do not use

With electrocautinary procedures, in the eyes

Stop use

If irritation and redness develop. If condition persists for more than 72 hours, consult a physician

Keep out of reach of children.

If swallowed, get medical help or contact a Poison Control Center right away

Directions

Wipe injection site vigorously and discard

Other information:

- Store at room temperature: 15° - 30° (59° - 86° F)
- Avoid excessive heat

Inactive Ingredient

Water

Principal Display Panel

NDC 76123-121-01

SH School Health®

Alcohol Prep Pads

Sterile

Medium 1.25 X 2.5 in (5.7 X 3.810 cm)

200/bx

Reorder# 49251

866.323.5465

www.schoolhealth.com